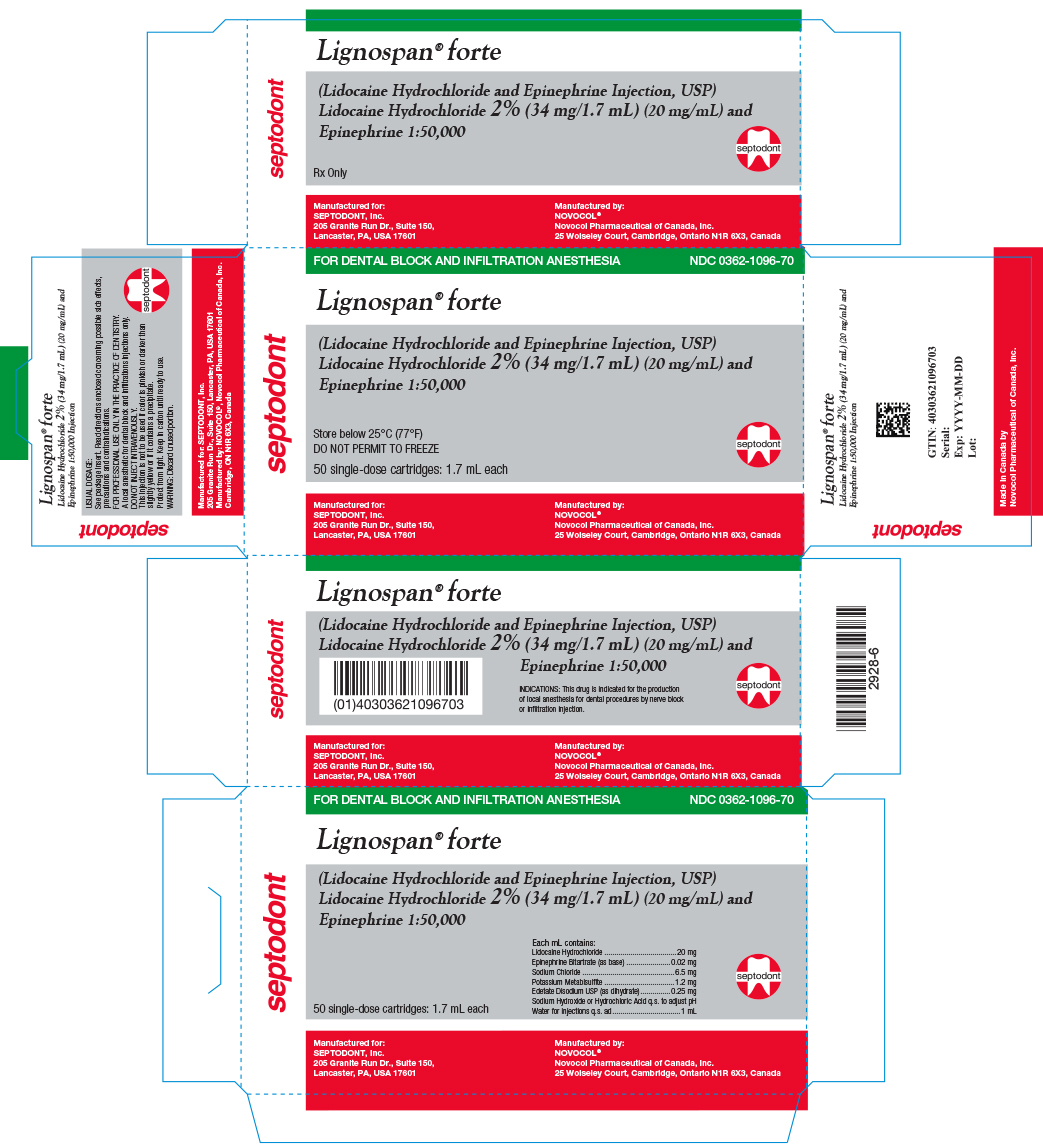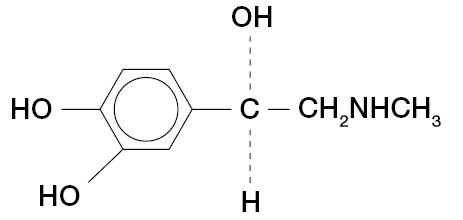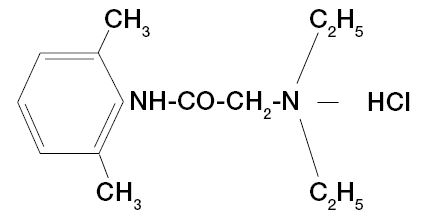 DRUG LABEL: Lignospan Forte
NDC: 0362-1096 | Form: INJECTION, SOLUTION
Manufacturer: Septodont, Inc.
Category: prescription | Type: HUMAN PRESCRIPTION DRUG LABEL
Date: 20250320

ACTIVE INGREDIENTS: Lidocaine Hydrochloride 20 mg/1 mL; Epinephrine Bitartrate  0.02 mg/1 mL
INACTIVE INGREDIENTS: Potassium Metabisulfite 1.2 mg/1 mL; Sodium Chloride 6.5 mg/1 mL; Edetate Disodium 0.25 mg/1 mL; Sodium Hydroxide; Water

LIGNOSPAN® (Lidocaine Hydrochloride and Epinephrine Injection, U.S.P.)
LIGNOSPAN FORTE (Lidocaine HCl 2% (34 mg/1.7 mL) (20 mg/mL) and Epinephrine 1:50,000 Injection)
LIGNOSPAN STANDARD (Lidocaine HCl 2% (34 mg/1.7 mL) (20 mg/mL) and Epinephrine 1:100,000 Injection)
Rx only
Solutions for local anesthesia in Dentistry

DESCRIPTION

LIGNOSPAN FORTE and LIGNOSPAN STANDARD are sterile isotonic solutions containing a local anesthetic agent, Lidocaine Hydrochloride, and a vasoconstrictor,
Epinephrine (as bitartrate) and are administered parenterally by injection. Both solutions are available in single dose cartridges of 1.7 mL (See INDICATIONS AND USAGE for specific uses). LIGNOSPAN Solutions contain lidocaine hydrochloride which is chemically designated as acetamide, 2-(diethylamino)-N-(2,6-dimethylphenyl)-monohydrochloride, and has the following structural formula:

C14H22N2O • HCl • H20 M.W. 288.8

Epinephrine is (-)-3,4-Dihydroxy-α-[(Methylamino) methyl] benzyl alcohol and has the following structural formula:

C9H13NO3 M.W. 183.21

COMPOSITION OF THE LIGNOSPAN INJECTIONS
BRAND NAME | PRODUCT IDENTIFICATION |  | FORMULA
 |  |  | SINGLE DOSE CARTRIDGE
 | Lidocaine hydrochloride | Epinephrine (as the bitartrate) | Sodium Chloride | Potassium metabisulfite | Edetate Disodium USP (as dihydrate)
 | Concentration % | Dilution | (mg/mL) | (mg/mL) | (mg/mL)
LIGNOSPAN FORTE | 2 | 1:50,000 | 6.5 | 1.2 | 0.25
LlGNOSPAN STANDARD | 2 | 1:100,000 | 6.5 | 1.2 | 0.25

The pH of the LIGNOSPAN FORTE and the LIGNOSPAN STANDARD solutions are adjusted to USP limits with Sodium Hydroxide or Hydrochloric Acid q.s. to adjust pH.

CLINICAL PHARMACOLOGY

Mechanism of action

Lidocaine stabilizes the neuronal membrane by inhibiting the ionic fluxes required for the initiation and conduction of nerve impulses, thereby effecting local anesthetic action.

Onset and duration of anesthesia

When used for infiltration anesthesia in dental patients, the time of onset averages less than two minutes for each of the two forms of LIGNOSPAN. LIGNOSPAN FORTE (lidocaine HCl 2% solution with a 1:50,000 epinephrine concentration) or LIGNOSPAN STANDARD (lidocaine HCl 2% solution with a 1:100,000 epinephrine concentration) provide an average pulp anesthesia of at least 60 minutes with an average duration of soft tissue anesthesia of approximately 2½ hours.

When used for nerve blocks in dental patients, the time of onset for both forms of LIGNOSPAN averages 2 - 4 minutes. LIGNOSPAN FORTE (lidocaine HCl 2% solution with a 1:50,000 epinephrine concentration) or LIGNOSPAN STANDARD (lidocaine HCl 2% solution with a 1:100,000 epinephrine concentration) provide pulp anesthesia averaging at least 90 minutes with an average duration of soft tissue anesthesia of 3 to 3½ hours.

Hemodynamics

Excessive blood levels may cause changes in cardiac output, total peripheral resistance, and mean arterial pressure. These changes may be attributable to a direct depressant effect of the local anesthetic agent on various components of the cardiovascular system and/or the beta-adrenergic receptor stimulating action of epinephrine when present.

Pharmacokinetics and metabolism

Information derived from diverse formulations, concentrations and usages reveals that lidocaine is completely absorbed following parenteral administration, its rate of absorption depending, for example, upon various factors such as the site of administration and the presence or absence of a vasoconstrictor agent. Except for intravascular administration, the highest blood levels are obtained following intercostal nerve block and the lowest after subcutaneous administration. The plasma binding of lidocaine is dependent on drug concentration, and the fraction bound decreases with increasing concentration. At concentration of 1 to 4 µg of free base per mL, 60 to 80 percent of lidocaine is protein bound. Binding is also dependent on the plasma concentration of the alpha-l-acid glycoprotein.

Lidocaine crosses the blood-brain and placental barriers, presumably by passive diffusion.

Lidocaine is metabolized rapidly by the liver, and metabolites and unchanged drug are excreted by the kidneys. Biotransformation includes oxidative N-dealkylation, ring hydroxylation, cleavage of the amide linkage, and conjugation. N- dealkylation, a major pathway of biotransformation, yields the metabolites monoethylglycinexylidide and glycinexylidide. The pharmacological/toxicological actions of these metabolites are similar to, but less potent than those of lidocaine. Approximately 90% of lidocaine administered is excreted in the form of various metabolites, and less than 10% is excreted unchanged. The primary metabolite in urine is a conjugate of 4-hydroxy-2, 6-dimethylaniline.

Studies of lidocaine metabolism following intravenous bolus injections have shown that the elimination half-life of this agent is typically 1.5 to 2.0 hours. Because of the rapid rate at which lidocaine is metabolized, any condition that affects liver function may alter lidocaine kinetics. The half-life may be prolonged two-fold or more in patients with liver dysfunction. Renal dysfunction does not affect lidocaine kinetics but may increase the accumulation of metabolites.

Factors such as acidosis and the use of CNS stimulants and depressants affect the CNS levels of lidocaine required to produce overt systemic effects. Objective adverse manifestations become increasingly apparent with increasing venous plasma levels above 6.0 µg free base per mL. In the rhesus monkey, arterial blood levels of 18 - 21 µg/mL have been shown to be the threshold for convulsive activity.

INDICATIONS AND USAGE

LIGNOSPAN Solutions are indicated for the production of local anesthesia for dental procedures by nerve block or infiltration techniques. Only accepted procedures for these techniques as described in standard textbooks are recommended.

CONTRAINDICATIONS

LIGNOSPAN is contraindicated in patients with a known history of hypersensitivity to local anesthetics of the amide type or to any components of the injectable formulations.

WARNINGS

DENTAL PRACTITIONERS WHO EMPLOY LOCAL ANESTHETIC AGENTS SHOULD BE WELL VERSED IN DIAGNOSIS AND MANAGEMENT OF EMERGENCIES WHICH MAY ARISE FROM THEIR USE. RESUSCITATIVE EQUIPMENT, OXYGEN AND OTHER RESUSCITATIVE DRUGS SHOULD BE AVAILABLE FOR IMMEDIATE USE.

To minimize the likelihood of intravascular injection, aspiration should be performed before the local anesthetic solution is injected. If blood is aspirated, the needle must be repositioned until no return of blood can be elicited by aspiration. Note, however, that the absence of blood in the syringe does not assure that intravascular injection will be avoided.

Local anesthetic procedures should be used with caution when there is inflammation and/or sepsis in the region of the proposed injection.

LIGNOSPAN solutions contain potassium metabisulfite, a sulfite that may cause allergic-type reactions including anaphylactic symptoms and life-threatening or less severe asthmatic episodes in certain susceptible people. The overall prevalence of sulfite sensitivity in the general population is unknown and probably low. Sulfite sensitivity is seen more frequently in asthmatic than in non asthmatic people.

The American Heart Association has made the following recommendations regarding the use of local anesthetics with vasoconstrictors in patients with ischemic heart disease: “Vasoconstrictor agents should be used in local anesthesia solutions during dental practice only when it is clear that the procedure will be shortened or the analgesia rendered more profound. When a vasoconstrictor is indicated, extreme care should be taken to avoid intravascular injection. The minimum possible amount of vasoconstrictor should be used.” (Kaplan, EL, editor: Cardiovascular disease in dental practice, Dallas 1986, American Heart Association.)

Methemoglobinemia: Cases of methemoglobinemia have been reported in association with local anesthetic use. Although all patients are at risk for methemoglobinemia, patients with glucose-6-phosphate dehydrogenase deficiency, congenital or idiopathic methemoglobinemia, cardiac or pulmonary compromise, infants under 6 months of age, and concurrent exposure to oxidizing agents or their metabolites are more susceptible to developing clinical manifestations of the condition. If local anesthetics must be used in these patients, close monitoring for symptoms and signs of methemoglobinemia is recommended.

Signs of methemoglobinemia may occur immediately or may be delayed some hours after exposure and are characterized by a cyanotic skin discoloration and/or abnormal coloration of the blood. Methemoglobin levels may continue to rise; therefore, immediate treatment is required to avert more serious central nervous system and cardiovascular adverse effects, including seizures, coma, arrhythmias, and death. Discontinue LIGNOSPAN and any other oxidizing agents. Depending on the severity of the signs and symptoms, patients may respond to supportive care, i.e., oxygen therapy, hydration. A more severe clinical presentation may require treatment with methylene blue, exchange transfusion, or hyperbaric oxygen.

PRECAUTIONS

General

The safety and effectiveness of lidocaine depend on proper dosage, correct technique, adequate precautions and readiness for emergencies. Consult standard textbooks for specific techniques and precautions for various regional anesthetic procedures. Resuscitative equipment, oxygen and other resuscitative drugs should be available for immediate use (See WARNINGS AND ADVERSE REACTIONS).

The lowest dosage that results in effective anesthesia should be used to avoid high plasma levels and serious adverse effects. Repeated doses of lidocaine may cause significant increases in blood levels with each repeated dose due to slow accumulation of the drug or its metabolites. Tolerance to elevated blood levels varies with the status of the patient. Debilitated, elderly patients, acutely ill patients, and children should be given reduced doses commensurate with their age and physical condition.

If sedatives are employed to reduce patient apprehension, reduced doses should be used since local anesthetic agents, like sedatives, are central nervous system depressants which in combination may have an additive effect. Young children should be given minimal doses of each agent.

Lidocaine should be used with caution in patients with severe shock or heart block. Lidocaine should also be used with caution in patients with impaired cardiovascular function. Local anesthetic solutions containing a vasoconstrictor should be used with caution in areas of the body supplied by end arteries or having otherwise compromised blood supply. Patients with peripheral vascular disease and those with hypertensive vascular disease may exhibit exaggerated vasoconstrictor response. Ischemic injury (such as exfoliating or ulcerating lesions) or necrosis may result. Preparations containing a vasoconstrictor should be used with caution in patients during or following the administration of potent general anesthetic agents, since cardiac arrhythmias may occur under such conditions.

Cardiovascular and respiratory (adequacy of ventilation) vital signs and the patient’s state of consciousness should be monitored after each local anesthetic injection. Restlessness, anxiety tinnitus, dizziness, blurred vision, tremors, depression or drowsiness should alert the practitioner to the possibility of central nervous system toxicity. Signs and symptoms of depressed cardiovascular function may commonly result from a vasovagal reaction, particularly if the patient is in an upright position : placing the patient in the recumbent position is recommended when an adverse response is noted after injection of a local anesthetic (See ADVERSE REACTIONS - Cardiovascular System.) Vasovagal reactions may elicit a range of clinical manifestations, from prodrome signs of pre-syncope (e.g. lightheadedness, pallor, nausea, sweating, visual disturbances, weakness) to brief loss of consciousness (i.e. syncope).

Lidocaine should be used with caution in patients with hepatic disease, since amide-type local anesthetics are metabolized by the liver. Patients with severe hepatic disease, because of their inability to metabolize local anesthetics normally, are at greater risk of developing toxic plasma concentrations.

Many drugs used during the conduct of anesthesia are considered potential triggering agents for familial malignant hyperthermia. Since it is not known whether amide-type local anesthetics may trigger this reaction, and since the need for supplemental general anesthesia cannot be predicted in advance, it is suggested that a standard protocol for management should be available. Early unexplained signs of tachycardia, tachypnea, labile blood pressure and metabolic acidosis may precede temperature elevation. Successful outcome is dependent on early diagnosis, prompt discontinuance of the suspected triggering agent (s) and prompt treatment, including oxygen therapy, dantrolene (consult dantrolene sodium intravenous package insert before using) and other supportive measures.

Lidocaine should be used with caution in persons with known drug sensitivities. Patients allergic to para-aminobenzoic acid derivatives (procaine, tetracaine, benzocaine, etc.) have not shown cross sensitivity to lidocaine.

Use in the Head and Neck Area

Small doses of local anesthetics injected into the head and neck area, including retrobulbar, dental and stellate ganglion blocks, may produce adverse reactions similar to systemic toxicity seen with unintentional intravascular injections of larger doses. Confusion, convulsions, respiratory depression and/or respiratory arrest, and cardiovascular stimulation or depression have been reported. These reactions may be due to intra-arterial injection of the local anesthetic with retrograde flow to the cerebral circulation. Patients receiving these blocks should have their circulation and respiration monitored and be constantly observed. Resuscitative equipment and personnel for treating adverse reactions should be immediately available. Dosage recommendations should not be exceeded (See DOSAGE AND ADMINISTRATION).

Information for Patients/Patient Counseling Information

The patient should be informed of the possibility of temporary loss of sensation and muscle function following infiltration or nerve block injections.

The patient should be advised to exert caution to avoid inadvertent trauma to the lips, tongue, cheek mucosae or soft palate when these structures are anesthetized. The ingestion of food should therefore be postponed until normal function returns. The patient should be advised to consult the dentist if anesthesia persists or if a rash develops. Inform patients that use of local anesthetics may cause methemoglobinemia, a serious condition that must be treated promptly. Advise patients or caregivers to seek immediate medical attention if they or someone in their care experience the following signs or symptoms: pale, gray, or blue colored skin (cyanosis); headache; rapid heart rate; shortness of breath; lightheadedness; or fatigue.

Clinically Significant Drug Interactions

The administration of local anesthetic solutions containing epinephrine or norepinephrine to patients receiving monoamine oxidase inhibitors, tricyclic antidepressants or phenothiazines may produce severe prolonged hypotension or hypertension. Concurrent use of these agents should generally be avoided. In situations when concurrent therapy is necessary, careful patient monitoring is essential.

Concurrent administration of vasopressor drugs and ergot-type oxytocic drugs may cause severe, persistent hypertension or cerebrovascular accidents.

As the LIGNOSPAN STANDARD and the LIGNOSPAN FORTE solutions both contain a vasoconstrictor (epinephrine), concurrent use of either with a Beta-adrenergic blocking agent (propranolol, timolol, etc.) may result in dose- dependent hypertension and bradycardia with possible heart block.

Patients who are administered local anesthetics are at increased risk of developing methemoglobinemia when concurrently exposed to the following drugs, which could include other local anesthetics:

EXAMPLES OF DRUGS ASSOCIATED WITH METHEMOGLOBINEMIA:
Class | Examples
Nitrates/Nitrites | nitric oxide, nitroglycerin, nitroprusside, nitrous oxide
Local anesthetics | articaine, benzocaine, bupivacaine, lidocaine, mepivacaine, prilocaine, procaine, ropivacaine, tetracaine
Antineoplastic Agents | cyclophosphamide, flutamide, hydroxyurea, ifosfamide, rasburicase
Antibiotics | dapsone, nitrofurantoin, para-aminosalicylic acid, sulfonamides
Antimalarials | chloroquine, primaquine
Anticonvulsants | phenobarbital, phenytoin, sodium valproate
Other drugs | acetaminophen, metoclopramide, quinine, sulfasalazine

Drug/Laboratory test interactions

The intramuscular injection of lidocaine may result in an increase in creatine phosphokinase levels. Thus, the use of this enzyme determination, without isoenzyme separation, as a diagnostic test for the presence of acute myocardial infarction may be compromised by the intramuscular injection of lidocaine.

Carcinogenesis, mutagenesis, impairment of fertility

Studies of lidocaine in animals to evaluate the carcinogenic and mutagenic potential or the effect on fertility have not been conducted.

PREGNANCY

Teratogenic Effects: Reproduction studies have been performed in rats at doses up to 6.6 times the human dose and have revealed no evidence of harm to the fetus caused by lidocaine. There are, however, no adequate and well-controlled studies in pregnant women. Animal reproduction studies are not always predictive of human response. General consideration should be given to this fact before administering lidocaine to women of childbearing potential, especially during early pregnancy when maximum organogenesis takes place.

Nursing mothers

It is not known whether this drug is excreted in human milk. Because many drugs are excreted in human milk, caution should be exercised when lidocaine is administered to a nursing woman.

Pediatric use

Dosages in pediatric population should be reduced, commensurate with age, body weight and physical condition (See DOSAGE AND ADMINISTRATION).

ADVERSE REACTIONS

Adverse experiences following the administration of lidocaine are similar in nature to those observed with other amide-type local anesthetic agents. These adverse experiences are, in general, dose-related and may result from high plasma levels (which may be caused by excessive dosage, rapid absorption, unintended intravascular injection or slow metabolic degradation), injection technique, volume of injection, hypersensitivity, idiosyncrasy or diminished tolerance on the part of the patient. Serious adverse experiences are generally systemic in nature. The following types are those most commonly reported:

Central Nervous System

CNS manifestations are excitatory and/or depressant and may be characterized by lightheadedness, nervousness, apprehension, euphoria, confusion, dizziness, drowsiness, tinnitus, blurred or double vision, vomiting, sensations of heat, cold or numbness, twitching, tremors, convulsions, unconsciousness, respiratory depression and arrest. The excitatory manifestations may be very brief or may not occur at all, in which case the first manifestation of toxicity may be drowsiness merging into unconsciousness and respiratory arrest.

Drowsiness following the administration of lidocaine is usually an early sign of a high blood level of the drug and may occur as a consequence of rapid absorption.

Cardiovascular system

Cardiovascular manifestations in response to lidocaine are usually depressant and are characterized by bradycardia, hypotension, and cardiovascular collapse, which may lead to cardiac arrest. In addition the beta-adrenergic receptor- stimulating action of epinephrine may lead to excitatory cardiovascular responses, such as tachycardia, palpitations, and hypertension.

Signs and symptoms of depressed cardiovascular function may commonly result from a vasovagal reaction, particularly if the patient is in an upright position. Less commonly, they may result from a direct effect of the drug. Failure to recognize the premonitory signs such as sweating, a feeling of faintness, changes in pulse or sensorium may result in progressive cerebral hypoxia and seizure or serious cardiovascular catastrophe. Management consists of placing the patient in the recumbent position and ventilation with oxygen. Supportive treatment of circulatory depression may require the administration of intravenous fluids and, when appropriate, a vasopressor (e.g, ephedrine) as directed by the clinical situation.

Allergic reactions

Allergic reactions are characterized by cutaneous lesions, urticaria, edema, anaphylactoid reactions, or dyspnea due to bronchoconstriction. Allergic reactions as a result of sensitivity to lidocaine are extremely rare and, if they occur, should be managed by conventional means. The detection of sensitivity by skin testing is of doubtful value.

Neurologic reactions

The incidences of adverse reactions (e.g., persistent neurologic deficit) associated with the use of local anesthetics may be related to the technique employed, the total dose of local anesthetic administered, the particular drug used, the route of administration, and the physical condition of the patient.

Persistent paresthesias of the lips, tongue, and oral tissues have been reported with the use of lidocaine, with slow, incomplete, or no recovery. These post-marketing events have been reported chiefly following nerve blocks in the mandible and have involved the trigeminal nerve and its branches.

OVERDOSAGE

Acute emergencies from local anesthetics are generally related to high plasma levels encountered during therapeutic use of local anesthetics or to unintended subarachnoid injection of local anesthetic solution (See ADVERSE REACTIONS, WARNINGS AND PRECAUTIONS).

Management of local anesthetic emergencies

The first consideration is prevention, best accomplished by careful and constant monitoring of cardiovascular and respiratory vital signs and the patient’s state of consciousness after each local anesthetic injection. At the first sign of change, oxygen should be administered.

The first step in the management of convulsions consists of immediate attention to the maintenance of a patent airway and assisted or controlled ventilation with oxygen and a delivery system capable of permitting immediate positive airway pressure by mask.

Immediately after the institution of these ventilatory measures, the adequacy of the circulation should be evaluated, keeping in mind that drugs used to treat convulsions sometimes depress the circulation when administered intravenously. Should convulsions persist despite adequate respiratory support, and if the status of the circulation permits, small increments of an ultra-short acting barbiturate (such as thiopental or thiamylal) or a benzodiazepine (such as diazepam) may be administered intravenously. The clinician should be familiar, prior to use of local anesthetics, with these anticonvulsant drugs. Supportive treatment of clrculatory depression may require administration of intravenous fluids and, when appropriate, a vasopressor as directed by the clinical situation (e.g., ephedrine).

If not treated immediately, both convulsions and cardiovascular depression can result in hypoxia, acidosis, bradycardia, arrhythmias and cardiac arrest. If cardiac arrest should occur, standard cardio-pulmonary resuscitative measures should be instituted. Endotracheal intubation, employing drugs and techniques familiar to the clinician, may be indicated, after initial administration of oxygen by mask, if difficulty is encountered in the maintenance of a patent airway or if prolonged ventilatory support (assisted or controlled) is indicated.

Dialysis is of negligible value in the treatment of acute overdosage with lidocaine.

The intravenous LD50 of lidocaine HCl in female mice is 26 (21 - 31) mg/kg and the subcutaneous LD50 is 264 (203 - 304) mg /kg.

DOSAGE AND ADMINISTRATION

The dosage of LIGNOSPAN (lidocaine HCl and epinephrine) depends on the physical status of the patient, the area of the oral cavity to be anesthetized, the vascularity of the oral tissues, and the technique of anesthesia used. The least volume of solution that results in effective local anesthesia should be administered; time should be allowed between injections to observe the patient for manifestations of an adverse reaction. For specific techniques and procedures of a local anesthesia in the oral cavity, refer to standard textbooks.

For most routine dental procedures, LIGNOSPAN STANDARD (lidocaine HCl 2% with a 1:100,000 epinephrine concentration) is preferred. However, when greater depth and a more pronounced hemostasis are required, LIGNOSPAN FORTE (lidocaine HCl 2 % with 1:50,000 epinephrine concentration) should be used.

Dosage requirements should be determined on an individual basis. In oral infiltration and / or mandibular block, initial dosages of 1.0 - 5.0 mL (½ to 2 ½ cartridges) of LIGNOSPAN (lidocaine HCl 2% solutions with a 1:50,000 or a 1:100,000 epinephrine concentration) are usually effective.

In children under 10 years of age, it is rarely necessary to administer more than one-half cartridge (0.9 - 1.0 mL or 18 - 20 mg of lidocaine) per procedure to achieve local anesthesia for a procedure involving a single tooth. In maxillary infiltration, this amount will often suffice to the treatment of two or even three teeth. In the mandibular block, however, satisfactory anesthesia achieved with this amount of drug, will allow treatment of the teeth of an entire quadrant. Aspiration is recommended since it reduces the possibility of intravascular injection, thereby keeping the incidence of side effects and anesthetic failures to a minimum. Moreover, injection should always be made slowly.

Maximum recommended dosages for LIGNOSPAN (lidocaine HCl 2% solutions with a 1:50,000 or a 1:100,000 epinephrine concentration).

Adult

For normal healthy adults, the amount of lidocaine HCl administered should be kept below 500 mg, and in any case, should not exceed 7 mg/kg (3.2 mg/lb) of body weight.

Pediatric

Pediatric patients: It is difficult to recommend a maximum dose of any drug for pediatric patients since this varies as a function of age and weight. For pediatric patients of less than ten years who have a normal lean body mass and normal body development, the maximum dose may be determined by the application of one of the standard pediatric drug formulas (e.g., Clark’s rule). For example, in pediatric patients of five years weighing 50 Ibs, the dose of lidocaine hydrochloride should not exceed 75 - 100 mg when calculated according to Clark’s rule. In any case, the maximum dose of lidocaine hydrochloride should not exceed 7 mg/kg (3.2 mg/lb) of body weight.

NOTE: Parenteral drug products should be inspected visually for particulate matter and discoloration prior to administration whenever the solution and container permit. Solutions that are discolored and / or contain particulate matter should not be used and any unused portion of a cartridge of LIGNOSPAN should be discarded.

HOW SUPPLIED

- LIGNOSPAN FORTE (Lidocaine hydrochloride 2% (34 mg/1.7 mL) (20 mg/mL) and Epinephrine 1:50,000 injection) is available in cardboard boxes containing 5 blisters of 10 x 1.7 mL single-dose cartridges (NDC 0362-1096-70).
- LIGNOSPAN STANDARD (Lidocaine hydrochloride 2% (34 mg/1.7 mL) (20 mg/mL) and Epinephrine 1:100,000 injection) is available in cardboard boxes containing 5 blisters of 10 x 1.7 mL single-dose cartridges (NDC 0362-1095-60).

STORAGE AND HANDLING

Store at controlled room temperature, below 25°C (77°F). Protect from light. Do not permit to freeze.

BOXES: For protection from light, retain in box until time of use. Once opened, the box should be reclosed by closing the end flap. Do not use if color is pinkish or darker than slightly yellow or if it contains a precipitate.

STERILIZATION : STORAGE AND TECHNICAL PROCEDURES

1. Cartridges should not be autoclaved, because the closures employed cannot withstand autoclaving temperatures and pressures.
2. If chemical disinfection of anesthetic cartridges is desired, either isopropyl alcohol (91%) or 70% ethyl alcohol is recommended. Many commercially available brands of rubbing alcohol, as well as solutions of ethyl alcohol not of U.S.P grade, contain denaturants that are injurious to rubber and, therefore, are not to be used. It is recommended that chemical disinfection be accomplished just prior to use by wiping the cartridge cap thoroughly with a pledge of cotton that has been moistened with recommended alcohol.
3. Certain metallic ions (mercury, zinc, copper, etc.) have been related to swelling and edema after local anesthesia in dentistry. Therefore, chemical disinfectants containing or releasing these ions are not recommended. Antirust tablets usually contain sodium nitrite or some similar agents that may be capable of releasing metal ions. Because of this, aluminium sealed cartridges should not be kept in such solutions.
4. Quaternary ammonium salts, such as benzalkonium chloride, are electrolytically incompatible with aluminium. Cartridges of LIGNOSPAN are sealed with aluminium caps and therefore should not be immersed in any solution containing these salts.
5. To avoid leakage of solutions during injection, be sure to penetrate the center of the rubber diaphragm when loading the syringe. An off-center penetration produces an oval shaped puncture that allows leakage around the needle. Other causes of leakage and breakage include badly worn syringes, aspirating syringes with bent harpoons, the use of syringes not designed to take 1.7 mL cartridges, and inadvertent freezing.
6. Cracking of glass cartridges is most often the result of an attempt to use a cartridge with an extruded plunger. An extruded plunger loses its lubrication and can be forced back into the cartridge only with difficulty. Cartridges with extruded plungers should be discarded.
7. Store at controlled room temperature, below 25°C (77°F)

Manufactured for SEPTODONT, Inc., 205 Granite Run Dr., Suite 150, Lancaster, PA, USA 17601
by Novocol Pharmaceutical of Canada Inc., 25 Wolseley Court, Cambridge, Ontario, Canada N1R 6X3

Rev. 03/2025 (2926-7)

PRINCIPAL DISPLAY PANEL - 1.7 mL Cartridge Carton

FOR DENTAL BLOCK AND INFILTRATION ANESTHESIA NDC 0362-1096-70

Lignospan® forte
(Lidocaine Hydrochloride and Epinephrine Injection, USP)
Lidocaine Hydrochloride 2% (34 mg/1.7 mL) (20 mg/mL) and Epinephrine 1:50,000

Store below 25°C (77°F)
DO NOT PERMIT TO FREEZE

50 single-dose cartridges: 1.7 mL each

Manufactured for SEPTODONT, Inc.
205 Granite Run Dr., Suite 150, Lancaster, PA, USA 17601
by Novocol Pharmaceutical of Canada Inc.
25 Wolseley Court, Cambridge, Ontario, Canada N1R 6X3